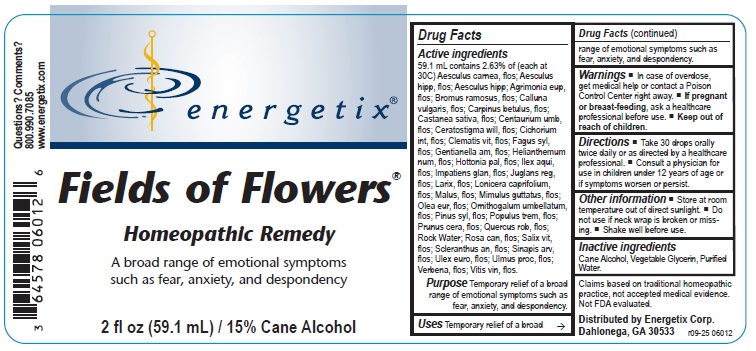 DRUG LABEL: Fields of Flowers
NDC: 64578-0105 | Form: LIQUID
Manufacturer: Energetix Corporation
Category: homeopathic | Type: HUMAN OTC DRUG LABEL
Date: 20251222

ACTIVE INGREDIENTS: AESCULUS CARNEA FLOWER 30 [hp_C]/59.1 mL; AESCULUS HIPPOCASTANUM FLOWER 30 [hp_C]/59.1 mL; HORSE CHESTNUT 30 [hp_C]/59.1 mL; AGRIMONIA EUPATORIA FLOWER 30 [hp_C]/59.1 mL; BROMUS RAMOSUS FLOWER 30 [hp_C]/59.1 mL; CALLUNA VULGARIS FLOWERING TOP 30 [hp_C]/59.1 mL; CARPINUS BETULUS FLOWERING TOP 30 [hp_C]/59.1 mL; CASTANEA SATIVA FLOWER 30 [hp_C]/59.1 mL; CENTAURIUM ERYTHRAEA FLOWER 30 [hp_C]/59.1 mL; CERATOSTIGMA WILLMOTTIANUM FLOWER 30 [hp_C]/59.1 mL; CICHORIUM INTYBUS FLOWER 30 [hp_C]/59.1 mL; CLEMATIS VITALBA FLOWER 30 [hp_C]/59.1 mL; FAGUS SYLVATICA FLOWERING TOP 30 [hp_C]/59.1 mL; GENTIANELLA AMARELLA FLOWER 30 [hp_C]/59.1 mL; HELIANTHEMUM NUMMULARIUM FLOWER 30 [hp_C]/59.1 mL; HOTTONIA PALUSTRIS FLOWER 30 [hp_C]/59.1 mL; ILEX AQUIFOLIUM FLOWERING TOP 30 [hp_C]/59.1 mL; IMPATIENS GLANDULIFERA FLOWER 30 [hp_C]/59.1 mL; JUGLANS REGIA FLOWERING TOP 30 [hp_C]/59.1 mL; LARIX DECIDUA FLOWERING TOP 30 [hp_C]/59.1 mL; LONICERA CAPRIFOLIUM FLOWERING TOP 30 [hp_C]/59.1 mL; MALUS DOMESTICA FLOWER 30 [hp_C]/59.1 mL; MIMULUS GUTTATUS FLOWERING TOP 30 [hp_C]/59.1 mL; OLEA EUROPAEA FLOWER 30 [hp_C]/59.1 mL; ORNITHOGALUM UMBELLATUM FLOWERING TOP 30 [hp_C]/59.1 mL; PINUS SYLVESTRIS FLOWERING TOP 30 [hp_C]/59.1 mL; POPULUS TREMULA FLOWERING TOP 30 [hp_C]/59.1 mL; PRUNUS CERASIFERA FLOWER 30 [hp_C]/59.1 mL; QUERCUS ROBUR FLOWER 30 [hp_C]/59.1 mL; ROSA CANINA FLOWER 30 [hp_C]/59.1 mL; SALIX ALBA FLOWERING TOP 30 [hp_C]/59.1 mL; SCLERANTHUS ANNUUS FLOWERING TOP 30 [hp_C]/59.1 mL; SINAPIS ARVENSIS FLOWERING/FRUITING TOP 30 [hp_C]/59.1 mL; ULEX EUROPAEUS FLOWER 30 [hp_C]/59.1 mL; ULMUS PROCERA FLOWERING TWIG 30 [hp_C]/59.1 mL; VERBENA OFFICINALIS FLOWERING TOP 30 [hp_C]/59.1 mL; VITIS VINIFERA FLOWERING TOP 30 [hp_C]/59.1 mL
INACTIVE INGREDIENTS: WATER; GLYCERIN; ALCOHOL

Fields of Flowers

ACTIVE INGREDIENT

Active ingredients 59.1 mL contains 2.63% of (each at 30C) Aesculus carnea, flos; Aesculus hipp, flos; Aesculus hipp; Agrimonia eup, flos; Bromus ramosus, flos; Calluna vulgaris, flos; Carpinus betulus, flos; Castanea sativa, flos; Centaurium umb, flos; Ceratostigma will, flos; Cichorium int, flos; Clematis vit, flos; Fagus syl, flos; Gentianella am, flos; Helianthemum num, flos; Hottonia pal, flos; Ilex aqui, flos; Impatiens glan, flos; Juglans reg, flos; Larix, flos; Lonicera caprifolium, flos; Malus, flos; Mimulus guttatus, flos; Olea eur, flos; Ornithogalum umbellatum, flos; Pinus syl, flos; Populus trem, flos; Prunus cera, flos; Quercus rob, flos; Rock Water; Rosa can, flos; Salix vit, flos; Scleranthus an, flos; Sinapis arv, flos; Ulex euro, flos; Ulmus proc, flos; Verbena, flos; Vitis vin, flos.

Claims based on traditional homeopathic practice, not accepted medical evidence. Not FDA evaluated.

INDICATIONS AND USAGE

UsesTemporary relief of a broad range of emotional symptoms such as fear, anxiety, and despondency.

Warnings

- In case of overdose, get medical help or contact a Poison Control Center right away.
- If pregnant or breast-feeding, ask a healthcare professional before use.

- Keep out of reach of children.

Directions

- Take 30 drops orally twice daily or as directed by a healthcare professional.
- Consult a physician for use in children under 12 years of age or if symptoms worsen or persist.

Other information

- Store at room temperature out of direct sunlight.
- Do not use if neck wrap is broken or missing.
- Shake well before use.

Inactive ingredients

Cane Alcohol, Vegetable Glycerin, Purified Water.

QUESTIONS

Distributed by Energetix Corp.

Dahlonega, GA 30533

Questions? Comments?

800.990.7085

www.energetix.com

PACKAGE LABEL

Fields of Flowers

Homeopathic Remedy

A broad range of emotional symptoms

such as fear, anxiety, and despondency

2 fl oz (59.1 mL) / 15% Cane Alcohol

PURPOSE

Purpose Temporary relief of a broad range of emotional symptoms such as fear, anxiety, and despondency.